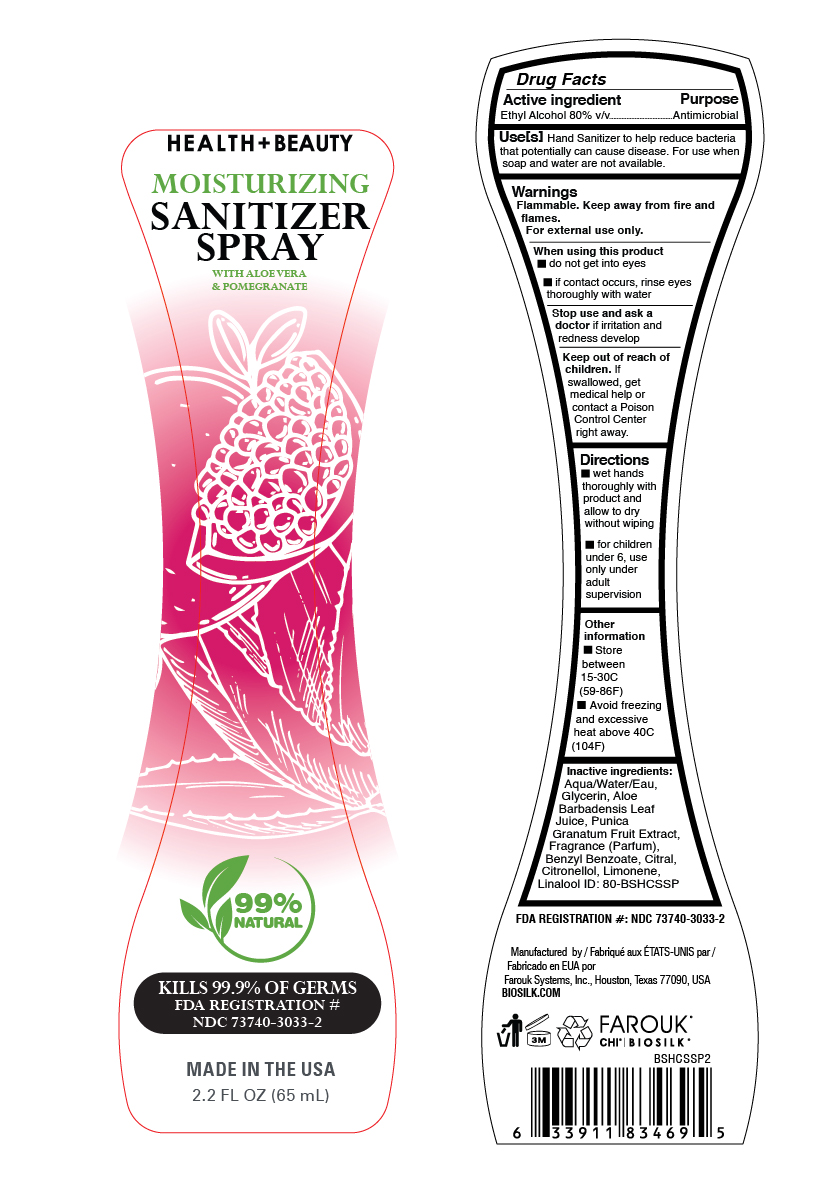 DRUG LABEL: Biosilk Health Beauty
NDC: 73740-3033 | Form: SPRAY
Manufacturer: Farouk Systems, Inc.
Category: otc | Type: HUMAN OTC DRUG LABEL
Date: 20201012

ACTIVE INGREDIENTS: ALCOHOL 80 g/100 g
INACTIVE INGREDIENTS: GLYCERIN 2 g/100 g; FRAGRANCE FLORAL ORC0902236 0.15648 g/100 g; CITRAL 0.00196 g/100 g; .BETA.-CITRONELLOL, (+/-)- 0.00392 g/100 g; BENZYL BENZOATE 0.00044 g/100 g; WATER 22.799 g/100 g; LINALOOL, (+/-)- 0.00294 g/100 g; LIMONENE, (+)- 0.03426 g/100 g; ALOE VERA LEAF 0.001 g/100 g

BioSilk Health Beauty Sanitizer Spray with Pomegranite

Active ingredient

Ethyl Alcohol 80% v/v

Stop use and ask a doctor

Stop use and ask a
doctor if irritation and
redness develop

Keep out of reach of children.

Keep out of reach of
children. If
swallowed, get
medical help or
contact a Poison
Control Center
right away.

Use[s]

Use[s] Hand Sanitizer to help reduce bacteria
that potentially can cause disease. For use when
soap and water are not available.

Stop use and ask a doctor

Stop use and ask a
doctor if irritation and
redness develop

When using this product

do not get into eyes
if contact occurs, rinse eyes
thoroughly with water

Directions

wet hands
thoroughly with
product and
allow to dry
without wiping
for children
under 6, use
only under
adult
supervision

Inactive ingredients:

Aqua/Water/Eau,
Glycerin, Aloe
Barbadensis Leaf
Juice, Punica
Granatum Fruit Extract,
Fragrance (Parfum),
Benzyl Benzoate, Citral,
Citronellol, Limonene,
Linalool

Directions

wet hands
thoroughly with
product and
allow to dry
without wiping
for children
under 6, use
only under
adult
supervision

Other information

Other
information
Store
between
15-30C
(59-86F)
Avoid freezing
and excessive
heat above 40C
(104F)

Warnings

Flammable. Keep away from fire and
flames.
For external use only.

Use[s]

Use[s] Hand Sanitizer to help reduce bacteria
that potentially can cause disease. For use when
soap and water are not available.

Biosilk Health + Beauty Moisturizing Sanitizer Spray with Aloe Vera & Pomegranate

99% Natural

Kills 99.9% of Germs

FDA Registration #

NDC 73740-3033-2

Made in the USA

2.2 FL OZ (65mL)